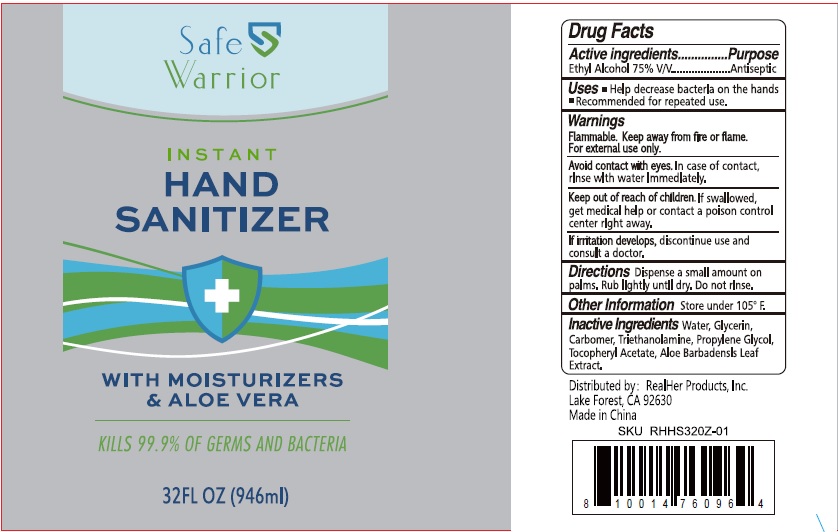 DRUG LABEL: Safe Warrior Instant Hand Sanitizer With Moisturizers and Aloe Vera
NDC: 74149-016 | Form: SOLUTION
Manufacturer: Yiwu Yangjie Daily Chemicals Co.,Ltd.
Category: otc | Type: HUMAN OTC DRUG LABEL
Date: 20200529

ACTIVE INGREDIENTS: alcohol 75 mL/100 mL
INACTIVE INGREDIENTS: WATER; PROPYLENE GLYCOL; ALOE VERA LEAF; CARBOMER 934; GLYCERIN; .ALPHA.-TOCOPHEROL ACETATE; TROLAMINE

Drug facts

Active ingredient - Ethyl Alcohol 75% V/V

Purpose - Antiseptic

KEEP OUT OF REACH OF CHILDREN

If swallowed, get medical help or contact a poison control center right away.

USES:

- Help decrease bacteria on the hands
- Recommended for repeated use

WARNINGS

For external use only.
Flammable. Keep away from fire or flame.

Avoid contact with eyes. In case of contact, rinse with water immediately.

If irritation develops, discontinue use and consult a doctor.

Directions:

Dispense a small amount on palms, rub lightly until dry. Do not rinse.

Other information:

Store under 105℉.

INACTIVE INGREDIENT

Water, Glycerin, Carbomer, Triethanolamine, Propylene Glycol, Tocopheryl Acetate, Aloe Barbadensis Leaf Extract